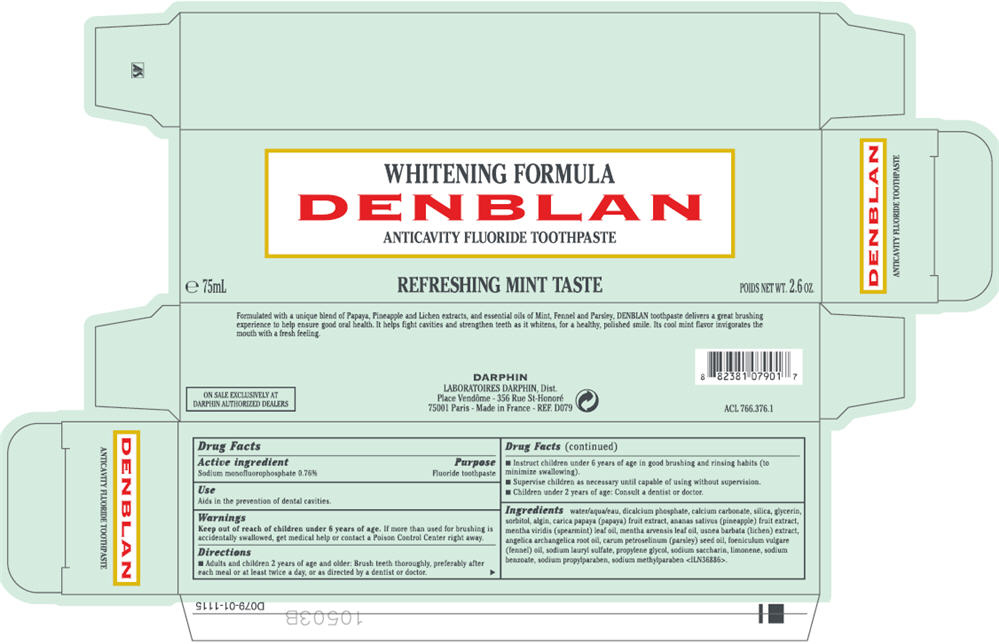 DRUG LABEL: DENBLAN 
NDC: 16555-996 | Form: PASTE, DENTIFRICE
Manufacturer: DARPHIN DIST.
Category: otc | Type: HUMAN OTC DRUG LABEL
Date: 20111201

ACTIVE INGREDIENTS: SODIUM MONOFLUOROPHOSPHATE 0.76 mL/100 mL
INACTIVE INGREDIENTS: WATER; ANHYDROUS DIBASIC CALCIUM PHOSPHATE; SILICON DIOXIDE; GLYCERIN; SORBITOL; PAPAYA; PINEAPPLE; SPEARMINT OIL; MENTHA ARVENSIS LEAF OIL; USNEA BARBATA; ANGELICA ROOT OIL; PARSLEY SEED OIL; FENNEL OIL; SODIUM LAURYL SULFATE; PROPYLENE GLYCOL; SACCHARIN SODIUM DIHYDRATE; SODIUM BENZOATE; PROPYLPARABEN SODIUM; METHYLPARABEN SODIUM

WHITENING FORMULA
DENBLAN
ANTICAVITY FLUORIDE TOOTHPASTE

Drug Facts

Active ingredient

Sodium monofluorophosphate 0.76%

Purpose

Fluoride toothpaste

Use

Aids in the prevention of dental cavities.

Warnings

Keep out of reach of children under 6 years of age.

WHEN USING

If more than used for brushing is accidentally swallowed, get medical help or contact a Poison Control Center right away.

Directions

- Adults and children 2 years of age and older: Brush teeth thoroughly, preferably after each meal or at least twice a day, or as directed by a dentist or doctor.
- Instruct children under 6 years of age in good brushing and rinsing habits (to minimize swallowing).
- Supervise children as neccessary until capable of using without supervision.
- Children under 2 years of age: Consult a dentist or doctor.

Ingredients

water, dicalcium phosphate, calcium carbonate, silica, glycerin, sorbitol, algin, carica papaya (papaya) fruit extract, ananas sativus (pineapple) fruit extract, mentha viridis (spearmint) leaf oil, mentha arvensis leaf oil, usnea barbata (lichen) extract, angelica archangelica root oil, carum petroselinum (parsley) seed oil, foeniculum vulgare (fennel) oil, sodium lauryl sulfate, propylene glycol, sodium saccharin, limonene, sodium benzoate, sodium propylparaben, sodium methylparaben <ILN36886>.

DARPHIN
LABORATORIES DARPHIN, Dist.

PRINCIPAL DISPLAY PANEL - 75mL Carton

WHITENING FORMULA
DENBLAN
ANTICAVITY FLUORIDE TOOTHPASTE

REFRESHING MINT TASTE

e 75mL
POIDS NET WT. 2.6 OZ.